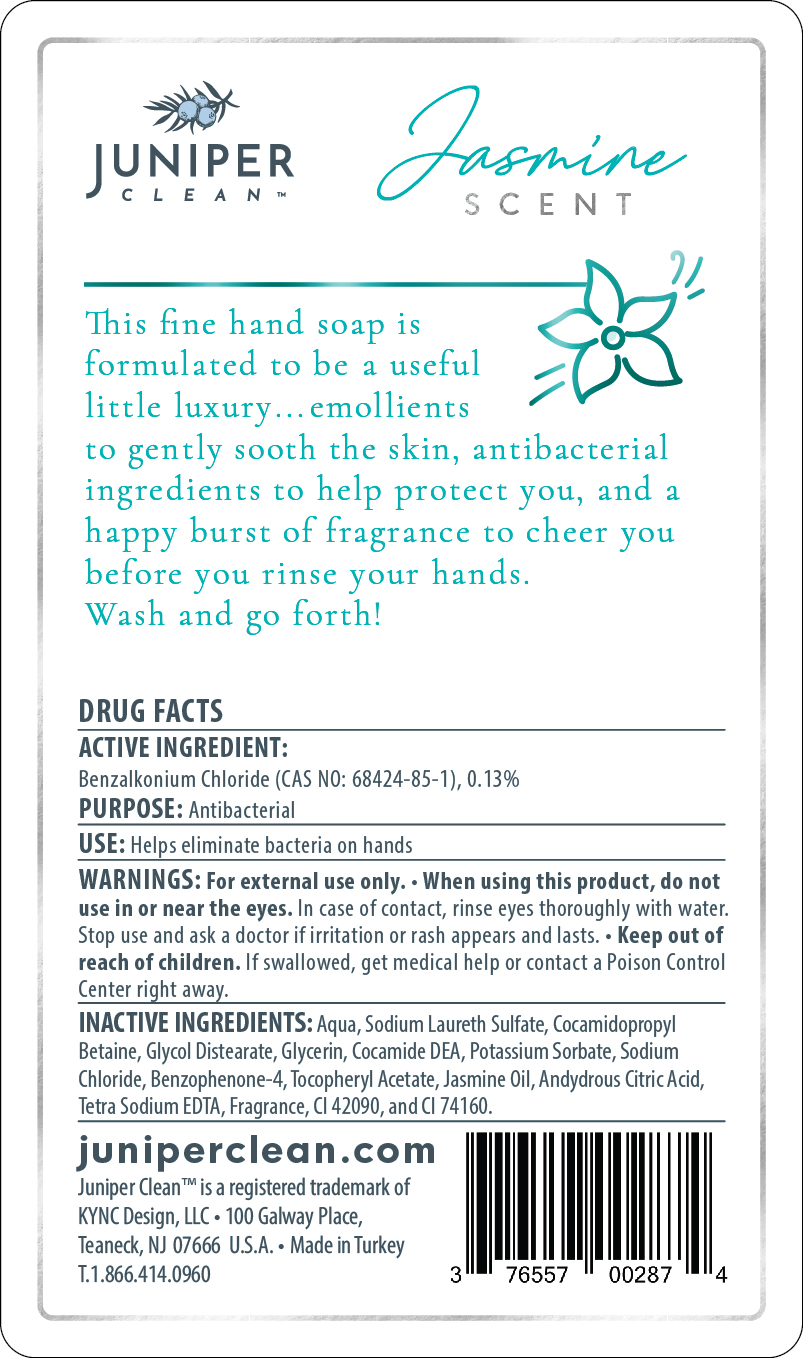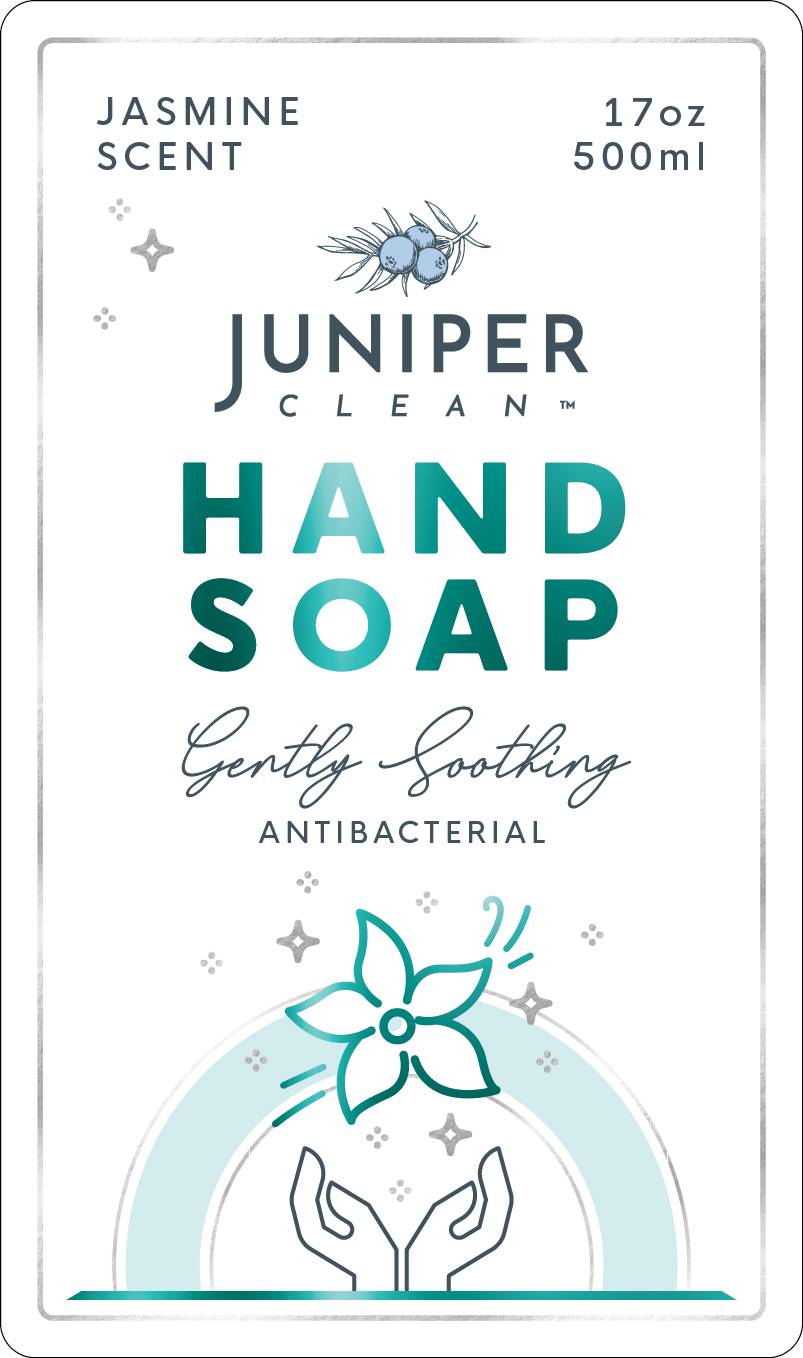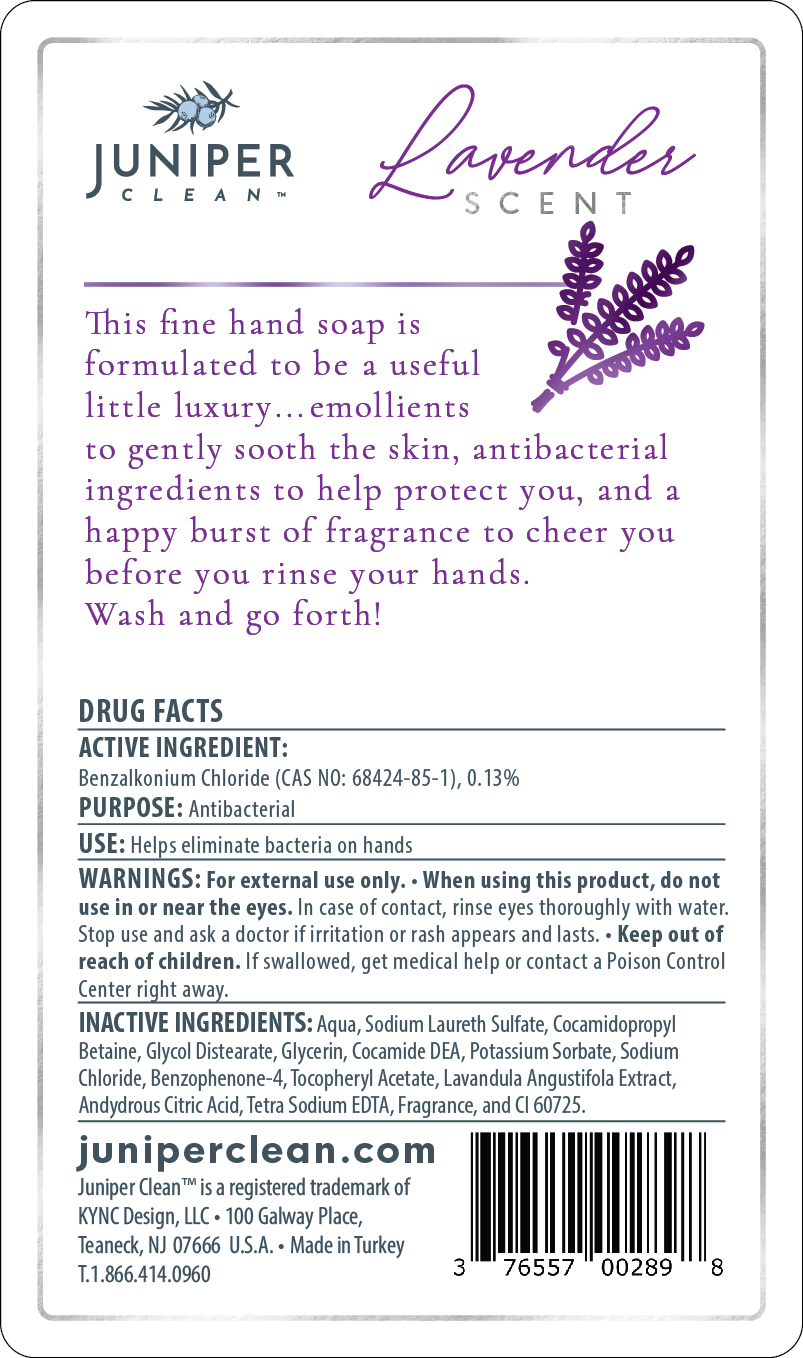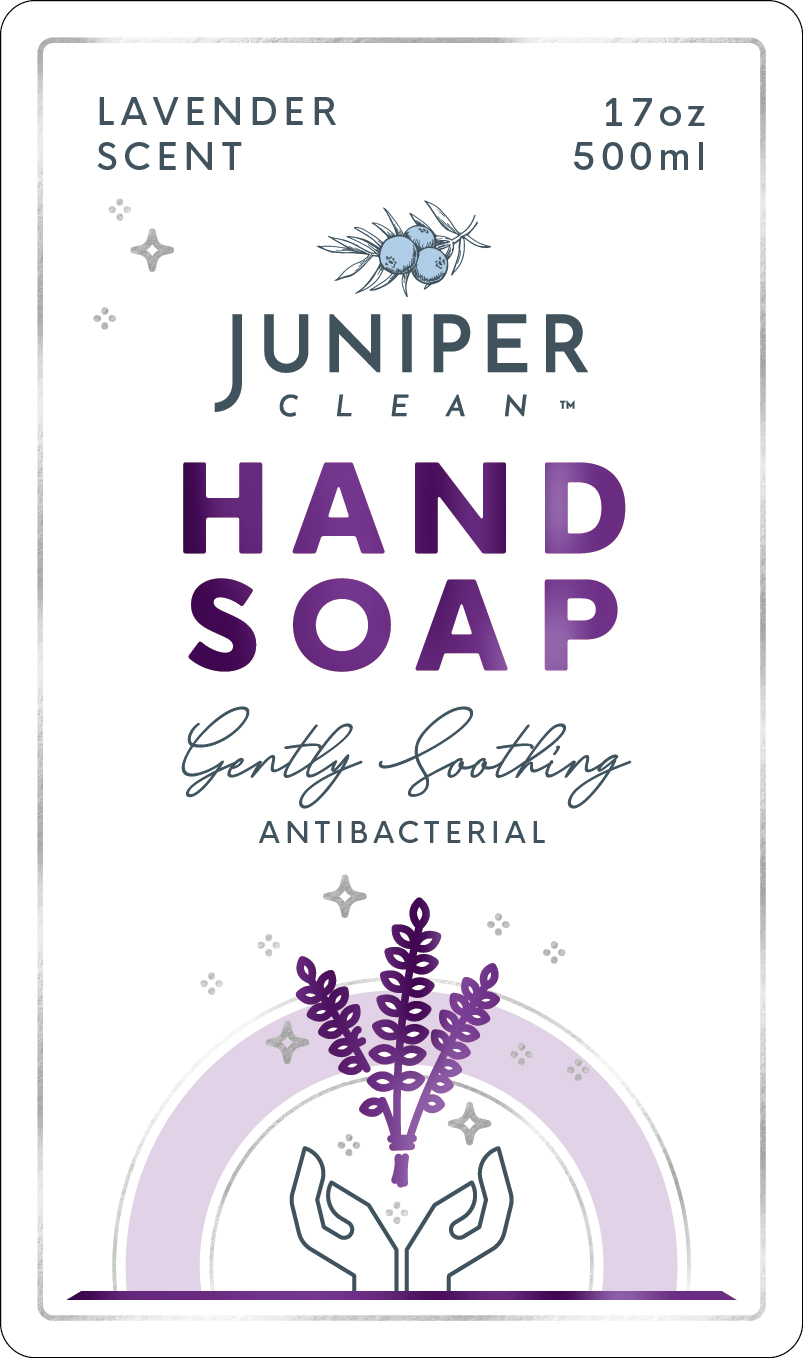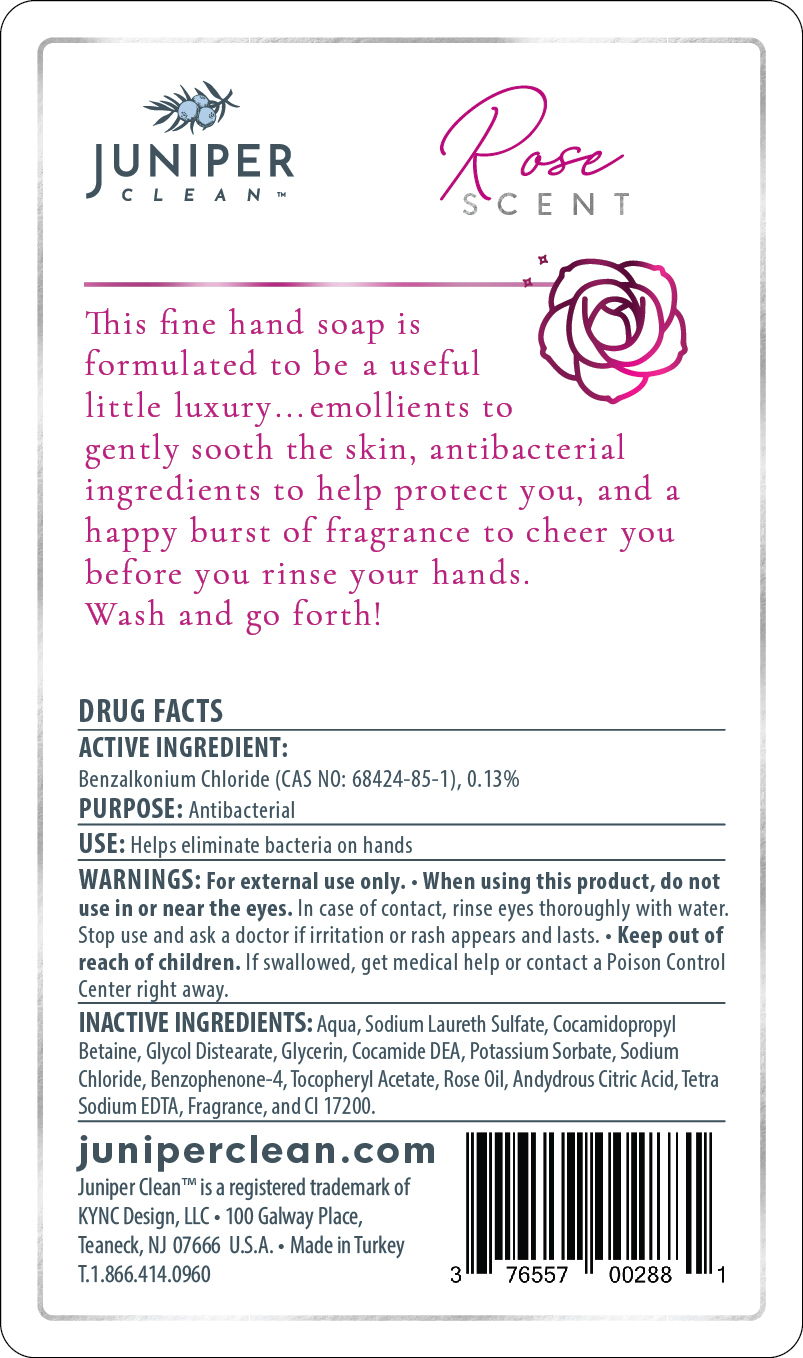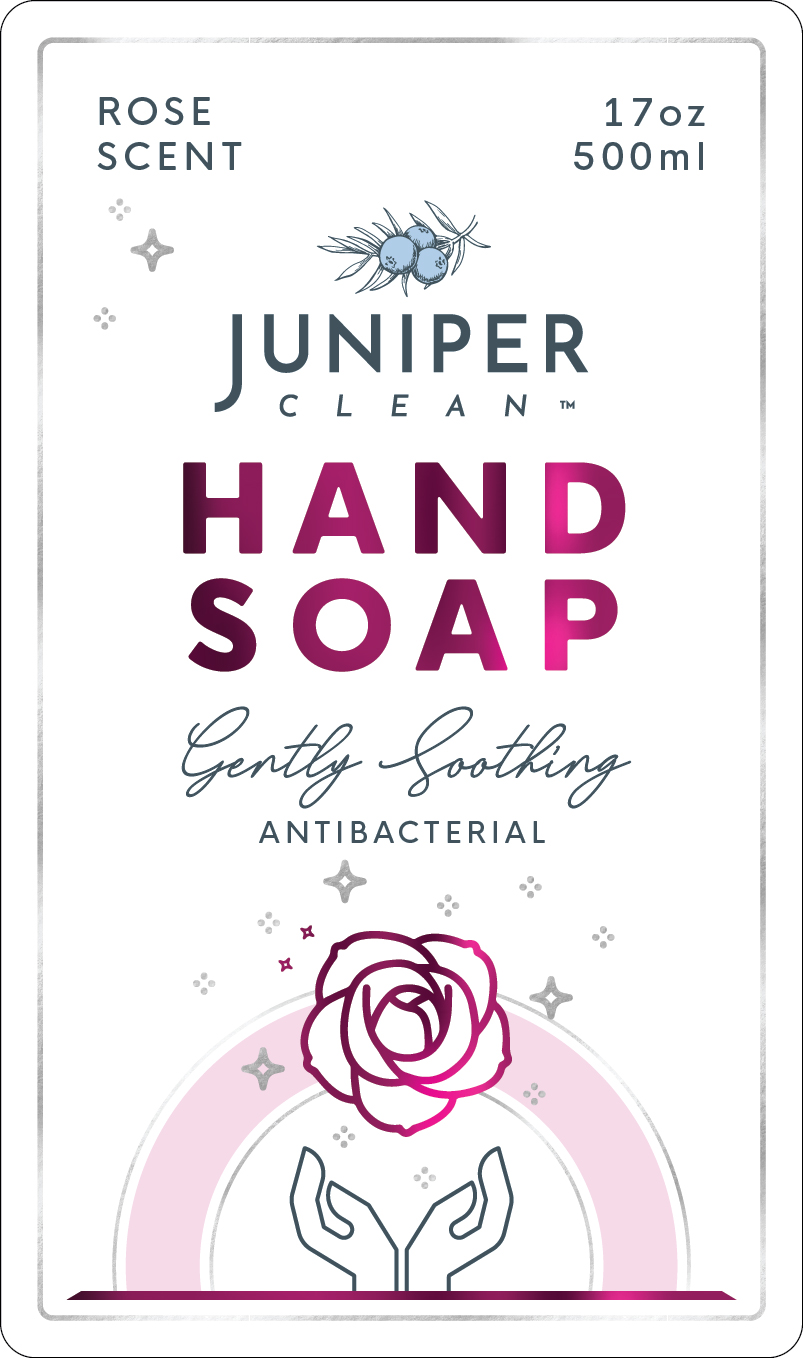 DRUG LABEL: JuniperClean Lavender
NDC: 76557-015 | Form: LIQUID
Manufacturer: KYNC Design LLC
Category: otc | Type: HUMAN OTC DRUG LABEL
Date: 20260123

ACTIVE INGREDIENTS: BENZALKONIUM CHLORIDE 0.13 g/100 g
INACTIVE INGREDIENTS: COCAMIDOPROPYL BETAINE; COCAMIDE; WATER; GLYCERIN; GLYCOL DISTEARATE; SODIUM CHLORIDE; EDETATE SODIUM; SODIUM LAURETH SULFATE; LAVANDULA ANGUSTIFOLIA FLOWER; .ALPHA.-TOCOPHEROL ACETATE, D-; POTASSIUM SORBATE; BENZOPHENONE-4-ISOTHIOCYANATE; ANHYDROUS CITRIC ACID; D&C VIOLET NO. 2

Juniper Clean Hand Soap

Active Ingredient(s)

Benzalkonium Chloride (CAS NO: 68424-85-1), 0.13% .

Purpose

Antimicrobial

Use

Helps eliminate bacteria on hands

WARNINGS

For external use only.

Do not use

If you are allergic to any of the ingredients.

Stop use and ask a doctor

if irritation or rash occurs.

Do not use in or near the eyes.

In case of contact, rinse eyes thoroughly with water. Stop use and ask a doctor if irritation or rash appears and lasts.

Keep out of reach of children.

If swallowed, get medical help or contact a poison control center immediately.

Directions

Wash hands and rinse

Inactive ingredients

Aqua, Sodium Laureth Sulfate, Cocamidopropyl Betaine, Glycol Distearate, Glycerin, Cocamide DEA, Potassium Sorbate, Sodium Chloride, Benzophenone-4, Tocopheryl Acetate, Andydrous Citric Acid, Tetra Sodium EDTA, Fragrance, Colorant.

PURPOSE

Antibacterial